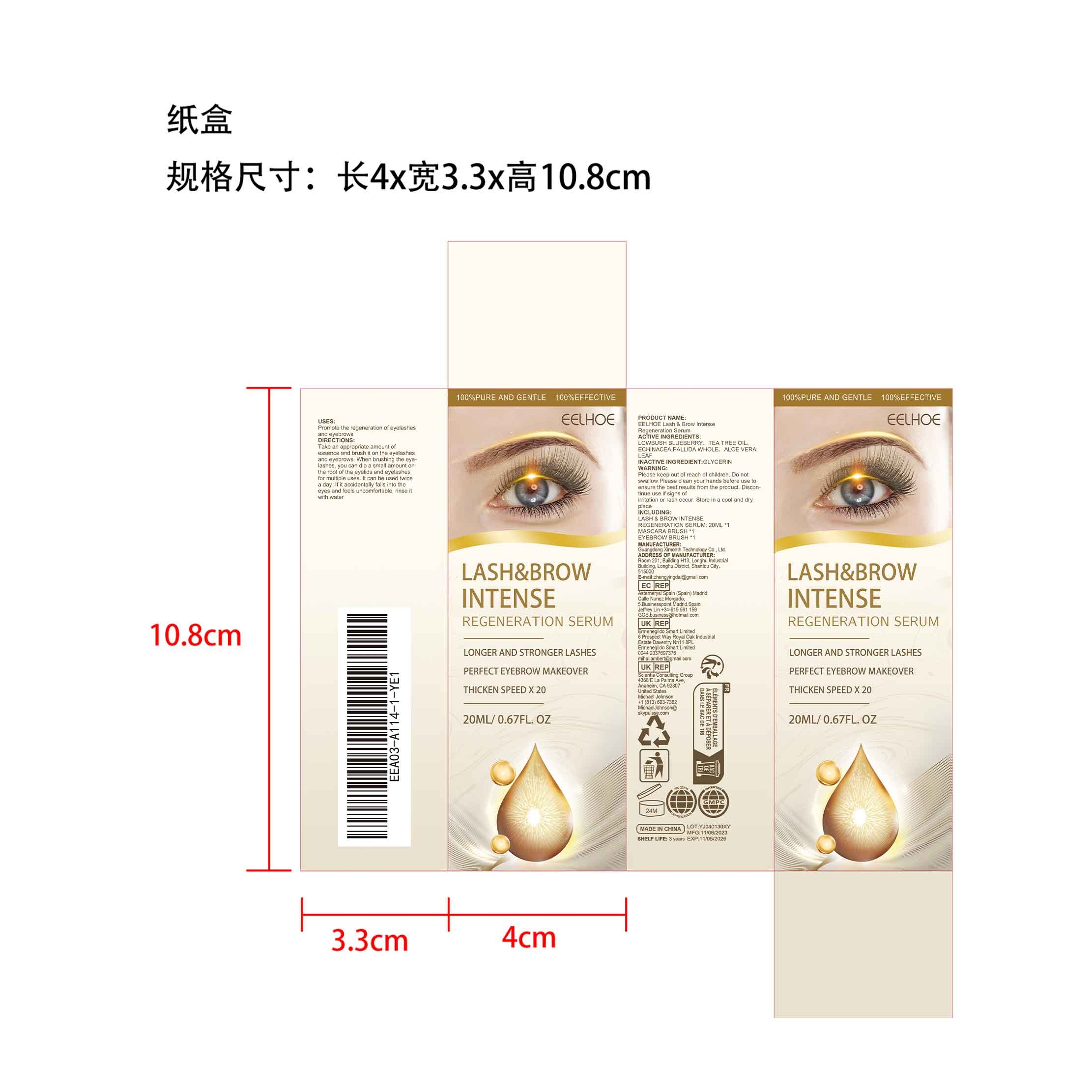 DRUG LABEL: EELHOE Lash Brow Intense Regeneration Serum
NDC: 84660-064 | Form: LIQUID
Manufacturer: Guangdong Ximonth Technology Co., Ltd.
Category: otc | Type: HUMAN OTC DRUG LABEL
Date: 20241102

ACTIVE INGREDIENTS: LOWBUSH BLUEBERRY 4 mg/20 mg; TEA TREE OIL 4 mg/20 mg; ALOE VERA LEAF 3 mg/20 mg; ECHINACEA PALLIDA WHOLE 4 mg/20 mg
INACTIVE INGREDIENTS: GLYCERIN 5 mg/20 mg

Active Ingredient(s)

LOWBUSH BLUEBERRY、TEA TREE OIL、ECHINACEA PALLIDA WHOLE、ALOE VERA LEAF

Purpose

Promote the regeneration of eyelashes and eyebrows

Use

Take an appropriate amount of essence and brush it on the eyelashes and eyebrows. When brushing the eyelashes, you can dip a small amount on the root of the eyelids and eyelashes for multiple uses. It can be used twice a day. If it accidentally falls into the eyes and feels uncomfortable, rinse it with water

Warning

Please keep out of reach of children.Do not swallow.Please clean your hands before use to ensure the best results from the product.Discontinue use if signs of irritation or rash occur.Store in a cool and dry place.

Do not use

Discontinue use if signs of irritation or rash occur.

Stop Use

Discontinue use if signs of irritation or rash occur.

KEEP OUT OF REACH OF CHILDREN

Please keep out of reach of children. Do not swallow.

STORAGE AND HANDLING

Store in a cool and dry place.

INACTIVE INGREDIENT

GLYCERIN